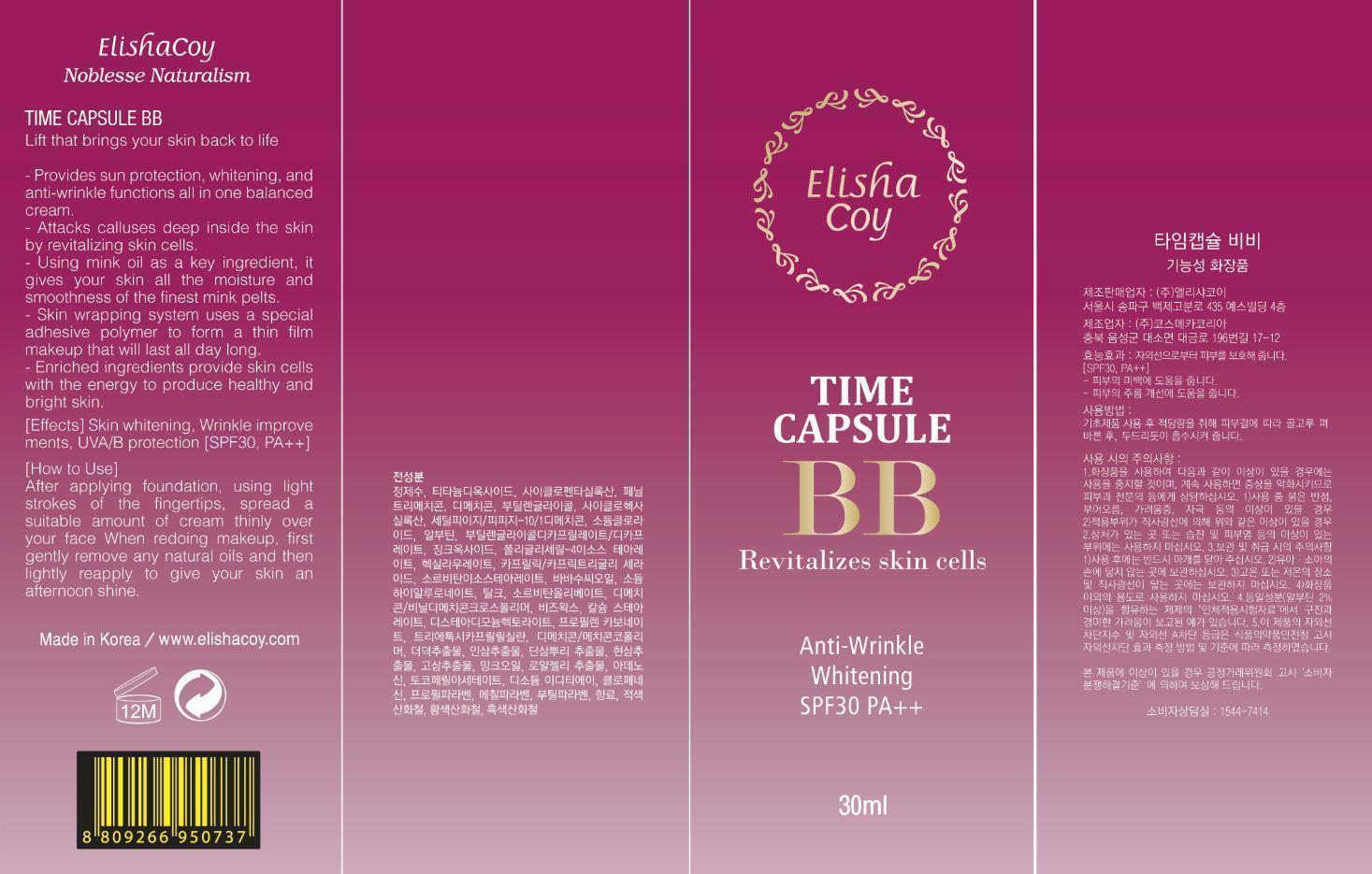 DRUG LABEL: Time Machine BB
NDC: 53727-103 | Form: CREAM
Manufacturer: Cosmecca Korea Co., Ltd.
Category: otc | Type: HUMAN OTC DRUG LABEL
Date: 20140815

ACTIVE INGREDIENTS: TITANIUM DIOXIDE 3 g/30 g; ZINC OXIDE 2 g/30 g
INACTIVE INGREDIENTS: WATER; CYCLOMETHICONE 5; PHENYL TRIMETHICONE; DIMETHICONE; BUTYLENE GLYCOL; CYCLOMETHICONE 6; CETYL PEG/PPG-10/1 DIMETHICONE (HLB 2); SODIUM CHLORIDE; ARBUTIN; BUTYLENE GLYCOL DICAPRYLATE/DICAPRATE; POLYGLYCERYL-4 ISOSTEARATE; HEXYL LAURATE; CAPRYLIC/CAPRIC/LAURIC TRIGLYCERIDE; SORBITAN ISOSTEARATE; BABASSU OIL; HYALURONATE SODIUM; TALC; SORBITAN OLIVATE; DIMETHICONE/VINYL DIMETHICONE CROSSPOLYMER (HARD PARTICLE); YELLOW WAX; CALCIUM STEARATE; DISTEARDIMONIUM HECTORITE; PROPYLENE CARBONATE; TRIETHOXYCAPRYLYLSILANE; DIMETHICONE/DIENE DIMETHICONE CROSSPOLYMER; CODONOPSIS LANCEOLATA ROOT; PANAX GINSENG ROOT OIL; SALVIA MILTIORRHIZA ROOT; SCROPHULARIA BUERGERIANA ROOT; SOPHORA FLAVESCENS ROOT; PALMITOLEIC ACID; ROYAL JELLY; ADENOSINE; .ALPHA.-TOCOPHEROL ACETATE; EDETATE DISODIUM; CHLORPHENESIN; PROPYLPARABEN; METHYLPARABEN; BUTYLPARABEN; FERRIC OXIDE RED

ACTIVE INGREDIENT

Titanium Dioxide (9.92%), Zinc Oxide (6.31%)

PURPOSE

Time Capsule BB

Revitalizes skin cells

Anti-Wrinkle

Whitening

SPF30 PA++

Keep out of reach of children.

INDICATIONS AND USAGE

ElishaCoy

Noblesse Naturalism

Time Capsule BB

Lift that brings your skin back to life

- Provides sun protection, whitening, and anti-wrinkle functions all in one balanced cream

- Attacks calluses deep inside the skin by revitalizing skin cells

- Using mink oil as a key ingredeint, it gives your skin all the moisture and smoothness of the finest mink pelts

- Skin wrapping system uses a special adhesive polymer to form a thin film makeup that will last all day long

- Enriched ingredients provide skin cells with the energy to produce healthy and bright skin

[Effects] Skin whitening, Wrinkle improve ments, UVA/B protection [SPF30 PA++]

Warnings

DOSAGE AND ADMINISTRATION

[How to Use]

After applying foundation, using light strokes of the fingertips, spread a suitable amount of cream thinly over your face When redoing makeup, first gently remove any natural oils and then lightly reapply to give your skin an afternoon shine.

INACTIVE INGREDIENT

Water, Cyclopentasiloxane, Phenyl Trimethicone, Dimethicone, Butylene Glycol, Cyclohexasiloxane, Cetyl PEG/PPG-10/1 Dimethicone, Sodium Chloride, Arbutin, Butylene Glycol Dicaprylate/Dicaprate, Polyglyceryl-4 Isostearate, Hexyl Laurate, Caprylic/Capric Triglyceride, Sorbitan Isostearate, Orbignya Oleifera Seed Oil, Sodium Hyaluronate, Talc, Sorbitan Olivate, Dimethicone/Vinyl Dimethicone, Crosspolymer, Beeswax, Calcium Stearate, Disteardimonium Hectorite, Propylene Carbonate, Triethoxycaprylylsilane, Dimethicone/Methicone Copolymer, Codonopsis Lanceolata Root Extract, Panax Ginseng Root Extract, Salvia Miltiorrhiza Root Extract, Scrophularia Buergeriana Root Extract, Sophora Angustifolia Root Extract, Mink Oil, Royal Jelly Extract, Adenosine, Tocopheryl Acetate, Disodium EDTA, Chlorphenesin, Propylparaben, Methylparaben, Butylparaben, Fragrance, Iron Oxides